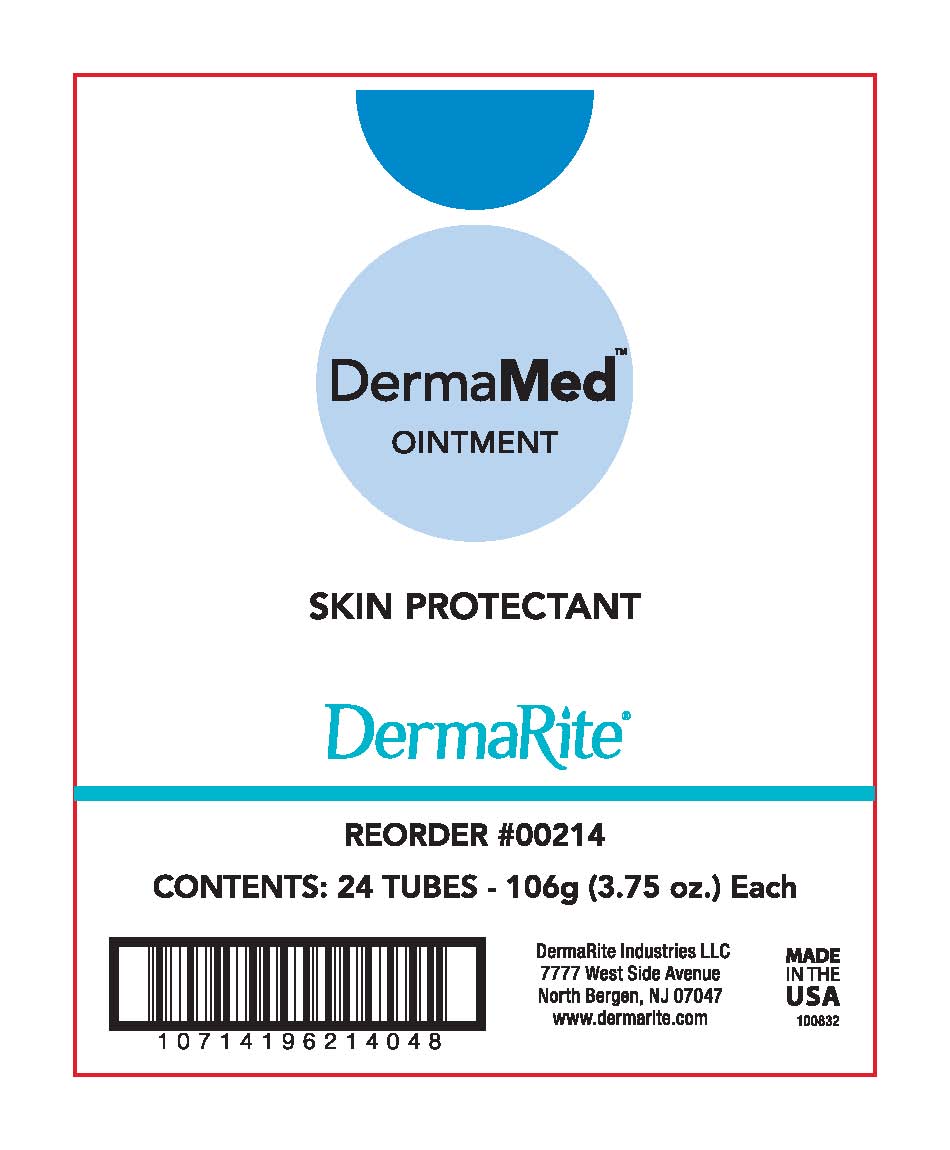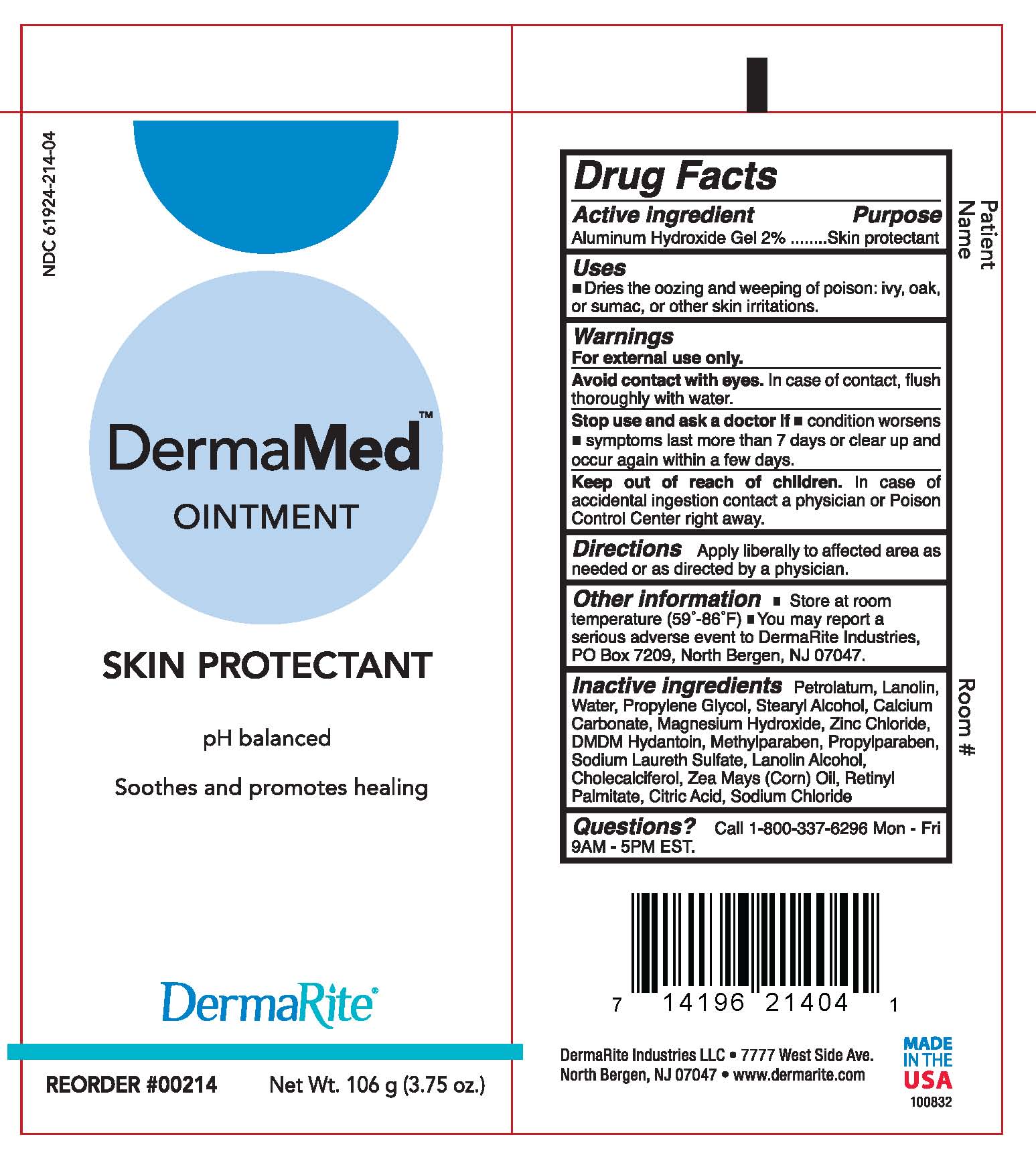 DRUG LABEL: DermaMed
NDC: 61924-214 | Form: OINTMENT
Manufacturer: DermaRite Industries, LLC
Category: otc | Type: HUMAN OTC DRUG LABEL
Date: 20241205

ACTIVE INGREDIENTS: ALUMINUM HYDROXIDE 2 g/100 g
INACTIVE INGREDIENTS: CHOLECALCIFEROL; LANOLIN; LANOLIN ALCOHOLS; SODIUM LAURETH SULFATE; MAGNESIUM HYDROXIDE; PROPYLENE GLYCOL 1-(2-METHYLBUTYRATE); VITAMIN A PALMITATE; DMDM HYDANTOIN; ANHYDROUS CITRIC ACID; CORN OIL; METHYLPARABEN; SODIUM CHLORIDE; ZINC CHLORIDE; PROPYLPARABEN; STEARYL ALCOHOL; PETROLATUM; CALCIUM CARBONATE; WATER

DermaMed

Active ingredient

Aluminum Hydroxide Gel 2%

Purpose

Skin protectant

Uses

Dries the oozing and weeping of poison: ivy, oak, or sumac, or other skin irritations.

Warnings

For external use only.

Avoid contact with eyes. In case of contact, flush thoroughly with water.

Warnings

Stop and ask a doctor if

- condition worsens
- symptoms last more than 7 days or clear up and occur again within a few days

Warnings

Keep out of reach of children.

In case of accidental ingestion contact a Physician or Poison Control Center right away.

Directions

Apply liberally to the affected area as needed or as directed by a physician.

Other information

- Store at room temperature (59º- 86ºF)
- You may report a serious adverse event to DermaRite Industries, PO Box 7209, North Bergen, NJ 07047.

Inactive ingredients

Petrolatum, Lanolin, Water, Propylene Glycol, Stearyl Alcohol, Calcium Carbonate, Magnesium Hydroxide, Zinc Chloride, DMDM Hydantoin, Methylparaben, Propylparaben, Sodium Laureth Sulfate, Lanolin Alcohol, Cholecalciferol, Zea Mays (Corn) Oil, Retinyl Palmitate, Citric Acid, Sodium Chloride

Questions?

Call 800-337-6296 Mon - Fri 9AM - 5PM EST.